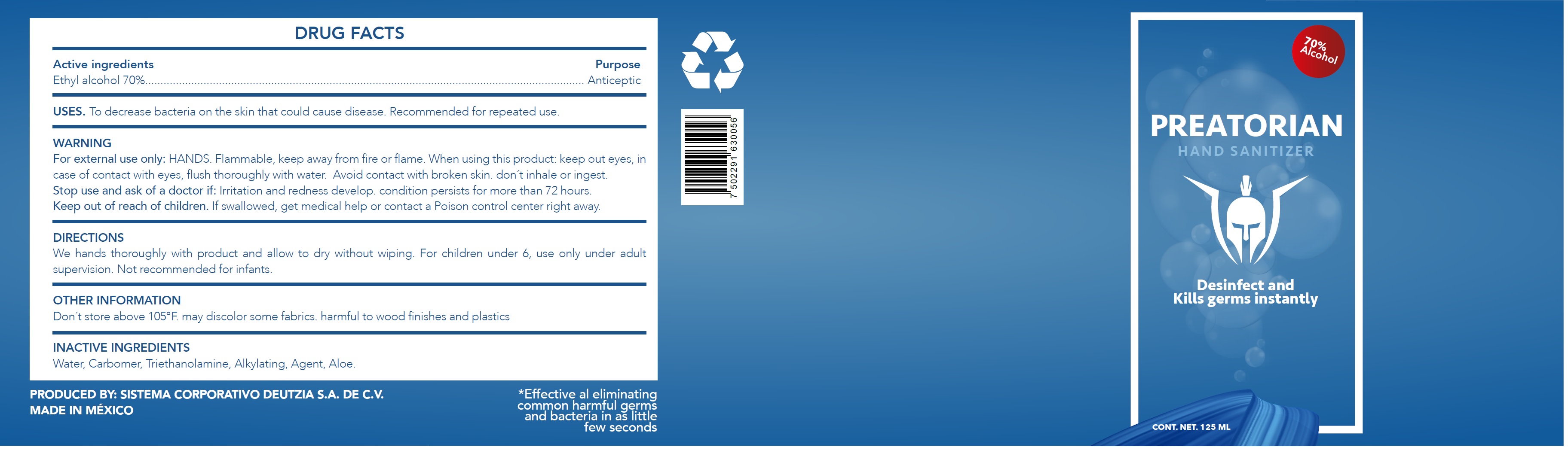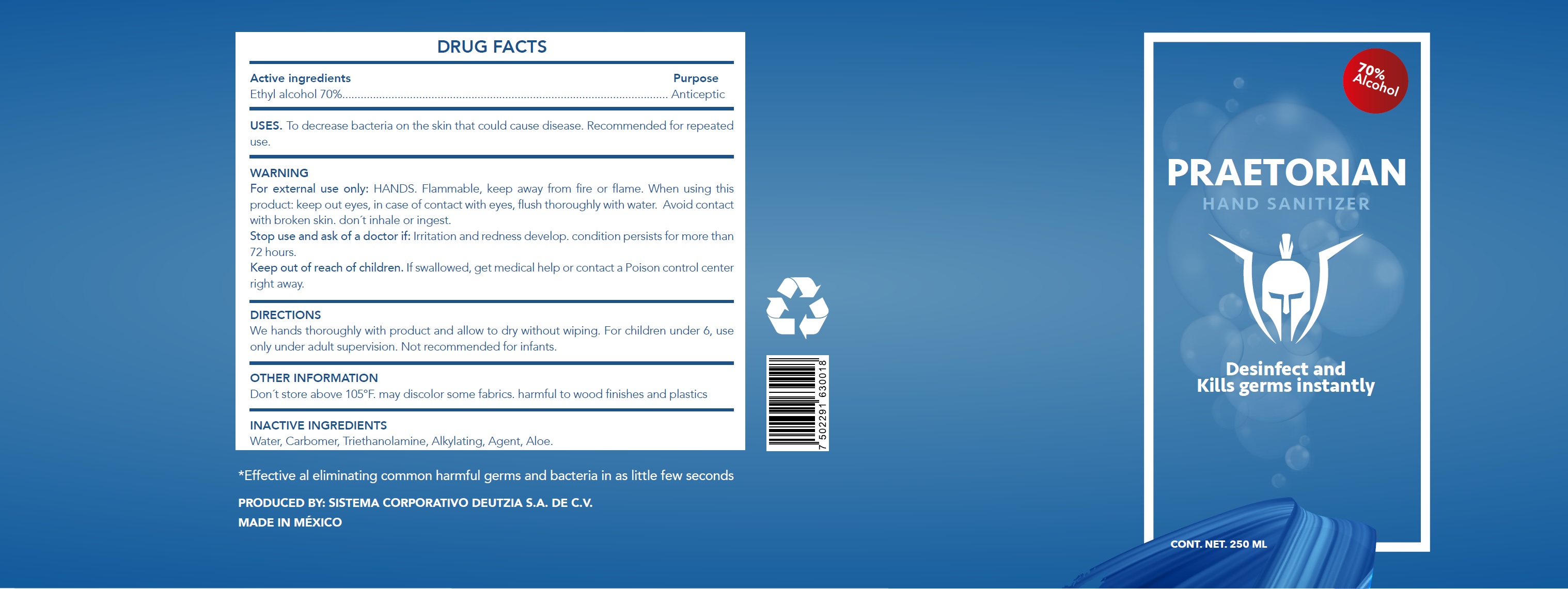 DRUG LABEL: Preatorian Hand Sanitizer
NDC: 80455-000 | Form: GEL
Manufacturer: Sistema Corporativo Deutzia, S.A. de C.V.
Category: otc | Type: HUMAN OTC DRUG LABEL
Date: 20200909

ACTIVE INGREDIENTS: ALCOHOL 0.7 mL/1 mL
INACTIVE INGREDIENTS: WATER; CARBOMER HOMOPOLYMER, UNSPECIFIED TYPE; TROLAMINE; ALOE VERA LEAF

Preatorian Hand Sanitizer

Active ingredients

Ethyl alcohol 70%

Purpose

Anticeptic

USES.

To decrease bacteria on the skin that could cause disease. Recommended for repeated use.

WARNING

For external use only: HANDS. Flammable, keep away from fire or flame.

When using this product:

keep out eyes, in case of contact with eyes, flush thoroughly with water. Avoid contact with broken skin. don´t inhale or ingest.

Stop use and ask of a doctor if:

Irritation and redness develop. condition persists for more than 72 hours.

Keep out of reach of children.

If swallowed, get medical help or contact a Poison control center right away.

DIRECTIONS

We hands thoroughly with product and allow to dry without wiping. For children under 6, use only under adult
supervision. Not recommended for infants.

OTHER INFORMATION

Don´t store above 105°F. may discolor some fabrics. harmful to wood finishes and plastics

INACTIVE INGREDIENTS

Water, Carbomer, Triethanolamine, Alkylating, Agent, Aloe.